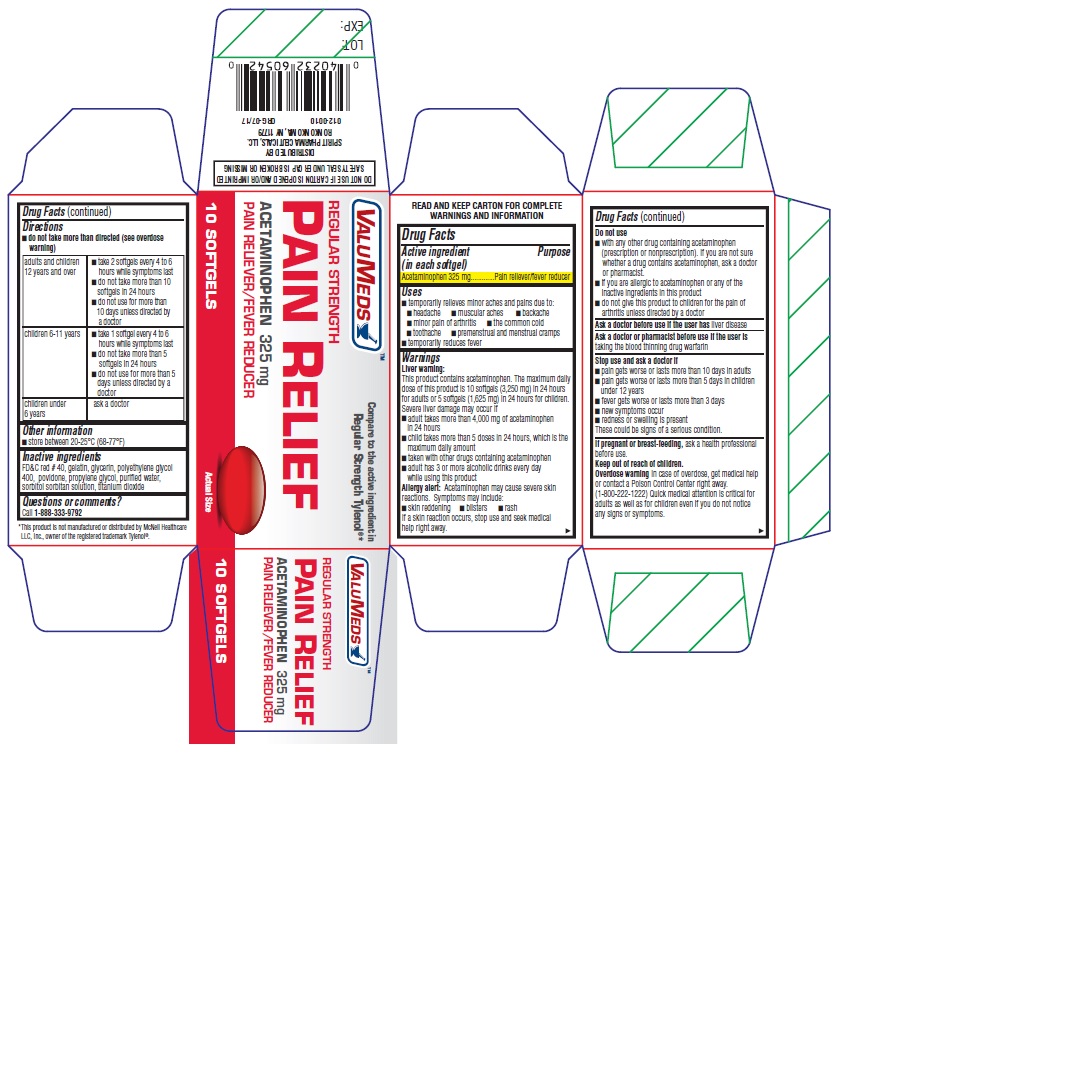 DRUG LABEL: REGULAR STRENGTH PAIN RELIEF
NDC: 68210-0120 | Form: CAPSULE, GELATIN COATED
Manufacturer: SPIRIT PHARMACEUTICALS LLC
Category: otc | Type: HUMAN OTC DRUG LABEL
Date: 20241212

ACTIVE INGREDIENTS: ACETAMINOPHEN 325 mg/1 1
INACTIVE INGREDIENTS: FD&C RED NO. 40; GELATIN, UNSPECIFIED; GLYCERIN; POLYETHYLENE GLYCOL, UNSPECIFIED; POVIDONE K30; PROPYLENE GLYCOL; WATER; SORBITOL; TITANIUM DIOXIDE

VALUMEDS™ REGULAR STRENGTH PAIN RELIEF

Drug Facts

Active ingredient (in each softgel)

Acetaminophen 325 mg

Purpose

Pain reliever/fever reducer

Uses

- temporarily relieves minor aches and pains due to:
  - headache
  - muscular aches
  - backache
  - minor pain of arthritis
  - the common cold
  - toothache
  - premenstrual and menstrual cramps
- temporarily reduces fever

Warnings

Liver warning

This product contains acetaminophen. The maximum daily dose of this product is 10 softgels (3,250 mg) in 24 hours for adults or 5 softgels (1,625 mg) in 24 hours for children. Severe liver damage may occur if

- adult takes more than 4,000 mg of acetaminophen in 24 hours
- child takes more than 5 doses in 24 hours, which is the maximum daily amount
- taken with other drugs containing acetaminophen
- adult has 3 or more alcoholic drinks every day while using this product

Allergy alert

Acetaminophen may cause severe skin reactions. Symptoms may include:

- skin reddening
- blisters
- rash

If a skin reaction occurs, stop use and seek medical help right away.

Do not use

- with any other drug containing acetaminophen (prescription or nonprescription). If you are not sure whether a drug contains acetaminophen, ask a doctor or pharmacist.
- if you are allergic to acetaminophen or any of the inactive ingredients in this product
- do not give this product to children for the pain of arthritis unless directed by a doctor

Ask a doctor before use if the user has liver disease

Ask a doctor or pharmacist before use if the user is taking the blood thinning drug warfarin

Stop use and ask a doctor if

- pain gets worse or lasts more than 10 days in adults
- pain gets worse or lasts more than 5 days in children under 12 years
- fever gets worse or lasts more than 3 days
- new symptoms occur
- redness or swelling is present

These could be signs of a serious condition.

PREGNANCY OR BREAST FEEDING

If pregnant or breast-feeding, ask a health professional before use.

Keep out of reach of children.

Overdose warning

In case of overdose, get medical help or contact a Poison Control Center right away. (1-800-222-1222) Quick medical attention is critical for adults as well as for children even if you do not notice any signs or symptoms.

Directions

- do not take more than directed (see overdose warning)

adults and children 12 years and over | - take 2 softgels every 4 to 6 hours while symptoms last - do not take more than 10 softgels in 24 hours - do not use for more than 10 days unless directed by a doctor
children 6-11 years | - take 1 softgel every 4 to 6 hours while symptoms last - do not take more than 5 softgels in 24 hours - do not use for more than 5 days unless directed by a doctor
children under 6 years | ask a doctor

Other information

- store between 20-25°C (68-77°F)

Inactive ingredients

FD&C red # 40, gelatin, glycerin, polyethylene glycol 400, povidone, propylene glycol, purified water, sorbitol sorbitan solution, titanium dioxide

Questions or comments?

Call 1-888-333-9792

DISTRIBUTED BY
SPIRIT PHARMACEUTICALS LLC.

RONKONKOMA, NY 11779

PRINCIPAL DISPLAY PANEL - 10 Softgel Bottle Carton

VALUMEDS™

COMPARE to the active ingredient in
REGULAR STRENGTH TYLENOL®*

REGULAR STRENGTH

PAIN RELIEF

Acetaminophen 325 mg

PAIN RELIEVER/FEVER REDUCER

10 softgels

Actual Size